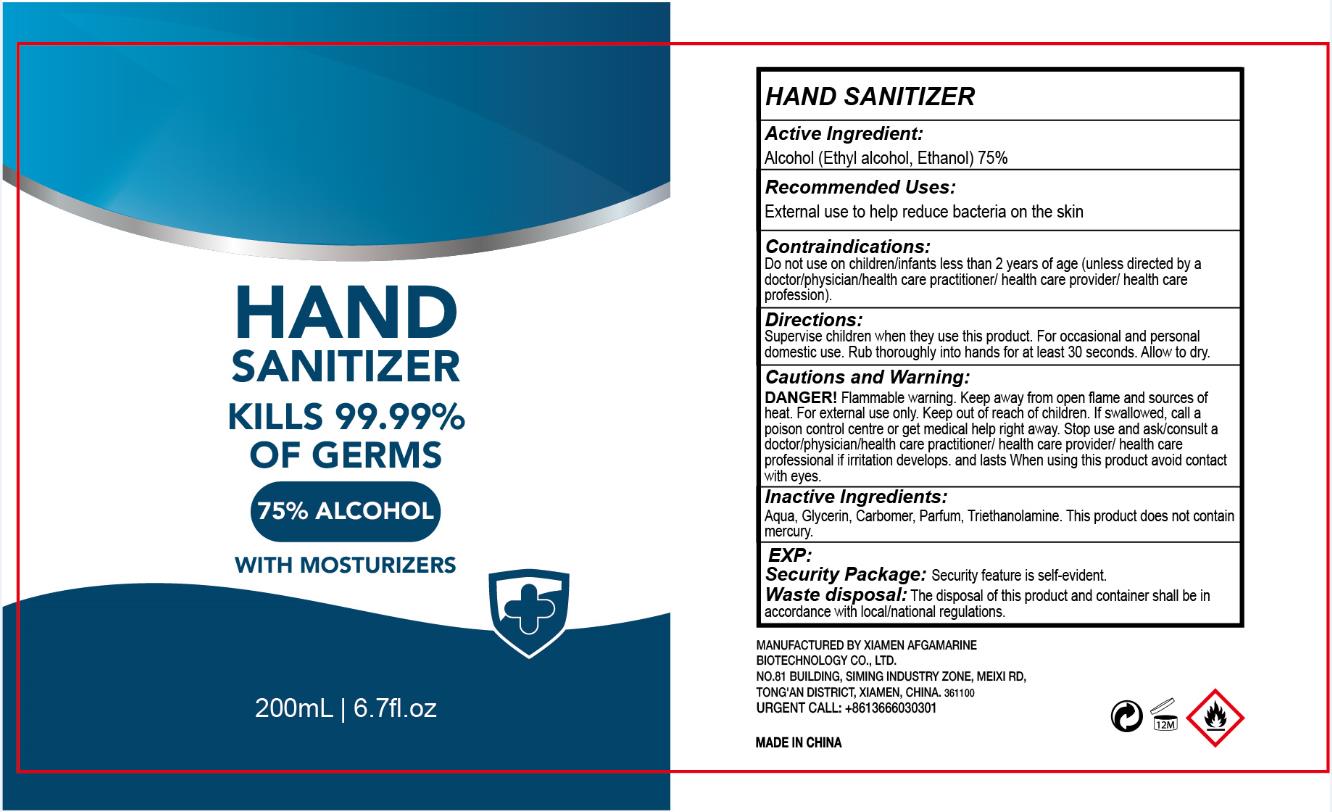 DRUG LABEL: Hand Sanitizer
NDC: 77607-100 | Form: GEL
Manufacturer: Xiamen Afgamarine Biotechnology Co., Ltd.
Category: otc | Type: HUMAN OTC DRUG LABEL
Date: 20200520

ACTIVE INGREDIENTS: ALCOHOL 75 mL/100 mL
INACTIVE INGREDIENTS: GLYCERIN; CARBOMER INTERPOLYMER TYPE A (ALLYL SUCROSE CROSSLINKED); WATER; DICHROSTACHYS CINEREA WHOLE; TROLAMINE

Afgamarine, Hand Sanitizer, Ethanol 75%, Gel

Active Ingredient(s)

Ethyl Alcohol 75% v/v. Purpose: Antimicrobial

Purpose

Antimicrobial.

Use

Recommended uses:

External use to help reduce bacteria on the skin.

Warnings

Cautions and Warning:

DANGER! Flammable warning. Keep away from open flame and sources of heat.
For external use only.

Do not use

Contraindications:

Do not use on children/infants less than 2 years of age (unless directed by a doctor/physician/health care practitioner/health care provider/health care profession).

When using this product avoid contact with eyes.

Stop use and ask/consult a doctor/physician/health care practitioner/health care provider/health care profession if irritation develops and lasts.

Keep out of reach of children. If swallowed, call a poison control center or get medical help right away.

Directions

Superise children when they use this product. For occasional and personal dosmetic use. Rub thoroughly into hands for at least 30 seconds. Allow to dry.

Other information

Security Package: Security feature is self-evident.

Waste disposal: The disposal of this product and container shall be in accordance with local/national regulations.

Inactive ingredients

Aqua, Glycerin, Carbomer, Parfum, Triethanolamine.